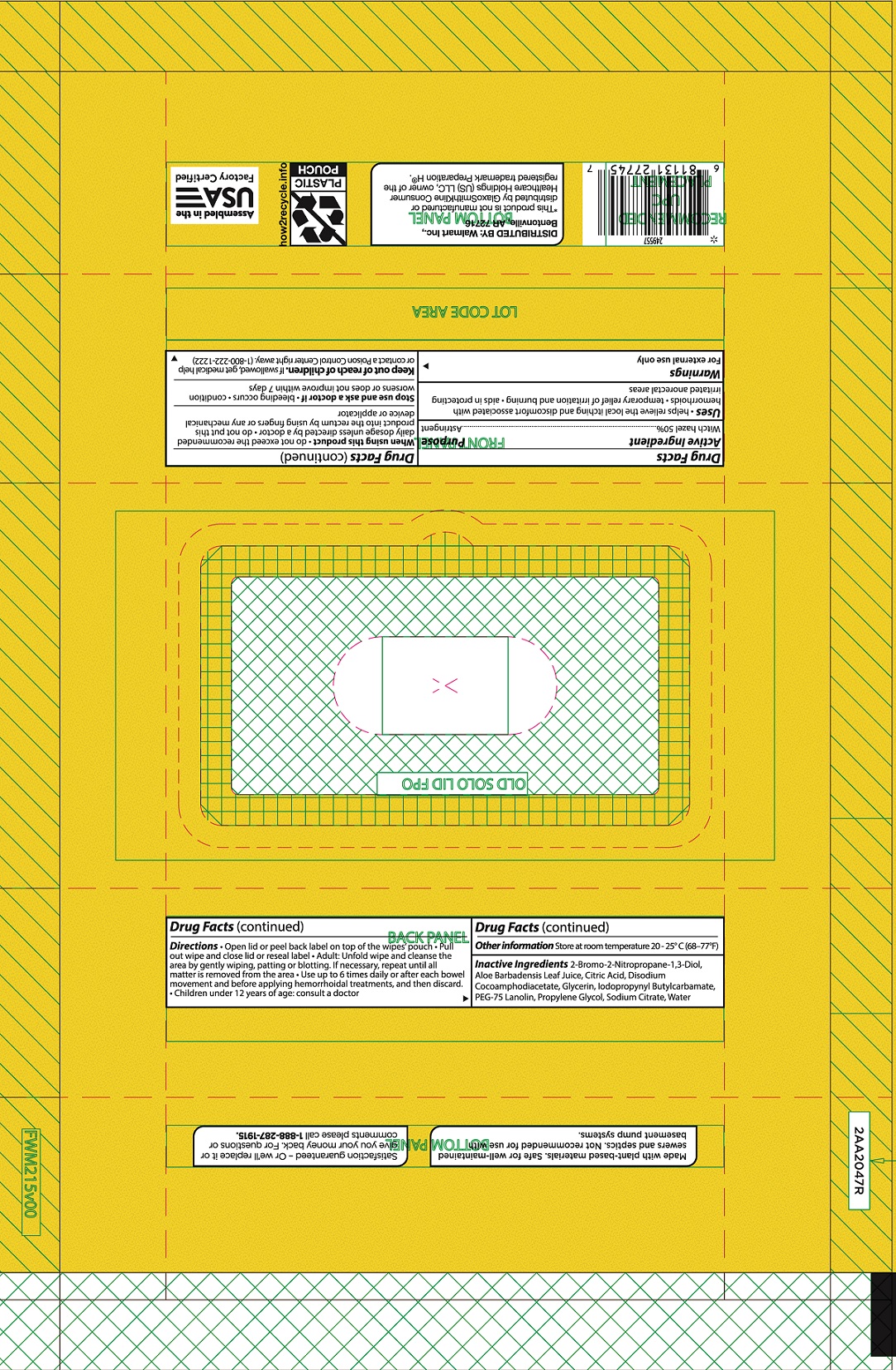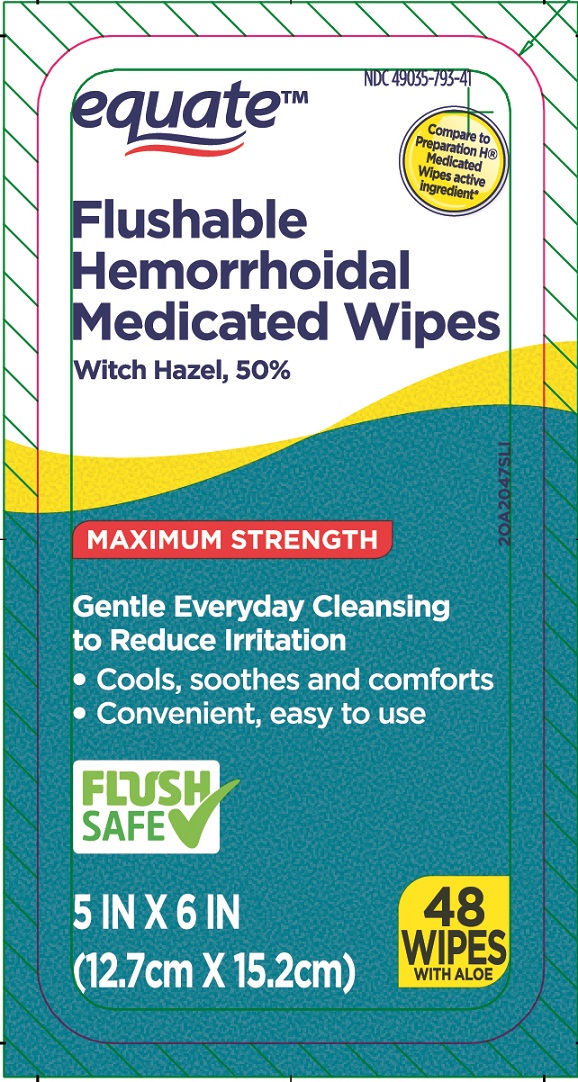 DRUG LABEL: Equate Hemorrhoidal Medicated Wipes
NDC: 49035-793 | Form: CLOTH
Manufacturer: Wal-Mart Stores, Inc.
Category: otc | Type: HUMAN OTC DRUG LABEL
Date: 20241107

ACTIVE INGREDIENTS: WITCH HAZEL 0.5 mg/1 mL
INACTIVE INGREDIENTS: WATER; GLYCERIN; PROPYLENE GLYCOL; SODIUM CITRATE; CITRIC ACID MONOHYDRATE; IODOPROPYNYL BUTYLCARBAMATE; DISODIUM COCOAMPHODIACETATE; BRONOPOL; ALOE VERA LEAF; PEG-75 LANOLIN

EQUATE FLUSHABLE HEMORRHOIDAL MEDICATED WIPES WITCH HAZEL, 50%

ACTIVE INGREDIENT

Witch hazel 50%

PURPOSE

Astringent

Uses

- helps relieve the local itching and discomfort associated with hemorrhoids
- temporary relief of irritation and burning
- aids in protecting irritated anorectal areas

WARNINGS

For external use only

WHEN USING THIS PRODUCT

- do not exceed the recommended daily dosage unless directed by a doctor
- do not put this product into the rectum by using fingers or any mechanical device or applicator

STOP USE AND ASK A DOCTOR IF

- bleeding occurs
- condition worsens or does not improve within 7 days

KEEP OUT OF REACH OF CHILDREN.

If swallowed, get medical help or contact a Poison Control Center right away.

DIRECTIONS

- adults: unfold wipe and cleanse the area by gently wiping, patting or blotting. If necessary, repeat until all matter is removed from the area
- use up to 6 times daily or after each bowel movement and before applying topical hemorrhoidal treatments, and then discard
- children under 12 years of age: consult a doctor

OTHER INFORMATION

- store at room temperature 20 - 25oC (68 - 77oF)

- for vaginal care - cleanse the area by gently wiping, patting or blotting. Repeat as needed.
- for use as a moist compress - if necessary, first cleanse the area as previously described. Fold wipe to desired size and place in contact with tissue for a soothing and cooling effect. Leave in place for up to 15 minutes and repeat as needed.

Inactive ingredients

2-Bromo-2-Nitropropane-1,3-Diol, Aloe Barbadensis Leaf Juice, Citric Acid, Disodium Cocoamphodiacetate, Glycerin, Iodopropynyl Butylcarbamate, PEG-75 Lanolin, Propylene Glycol, Sodium Citrate, Water

FOR COMMENTS OR QUESTIONS PLEASE

DISTRIBUTED BY:
WAL-MART STORES, INC.
BENTONVILLE, AR 72716
(C) Wal-Mart Stores, Inc.
*This product is not manufactured or distributed by Pfizer Consumer Healthcare, owner of the registered trademark Preparation H(R).
Satisfaction guaranteed - Or we'll replace it or give you your money back.
For questions or comments or to report an undesired reaction or side effect, please call 1-888-287-1915

PRINCIPAL DISPLAY PANEL - LID LABEL

Compare to Preparation H(R) Medicated Wipes Active Ingredient*

2OA694SLI

NDC 49035-793-41
equate

Flushable Hemorrhoidal

Medicated Wipes Witch Hazel, 50%

Gentle, Everyday Cleansing to Reduce Irritation

- Cools, soothes and comforts
- Convenient, easy to use

Flush

Safe

48

MEDICATED

WIPES

WITH ALOE
5 in x 6 in (12.7 cm x 15.2 cm)

Flowrap1

Lid1 Label